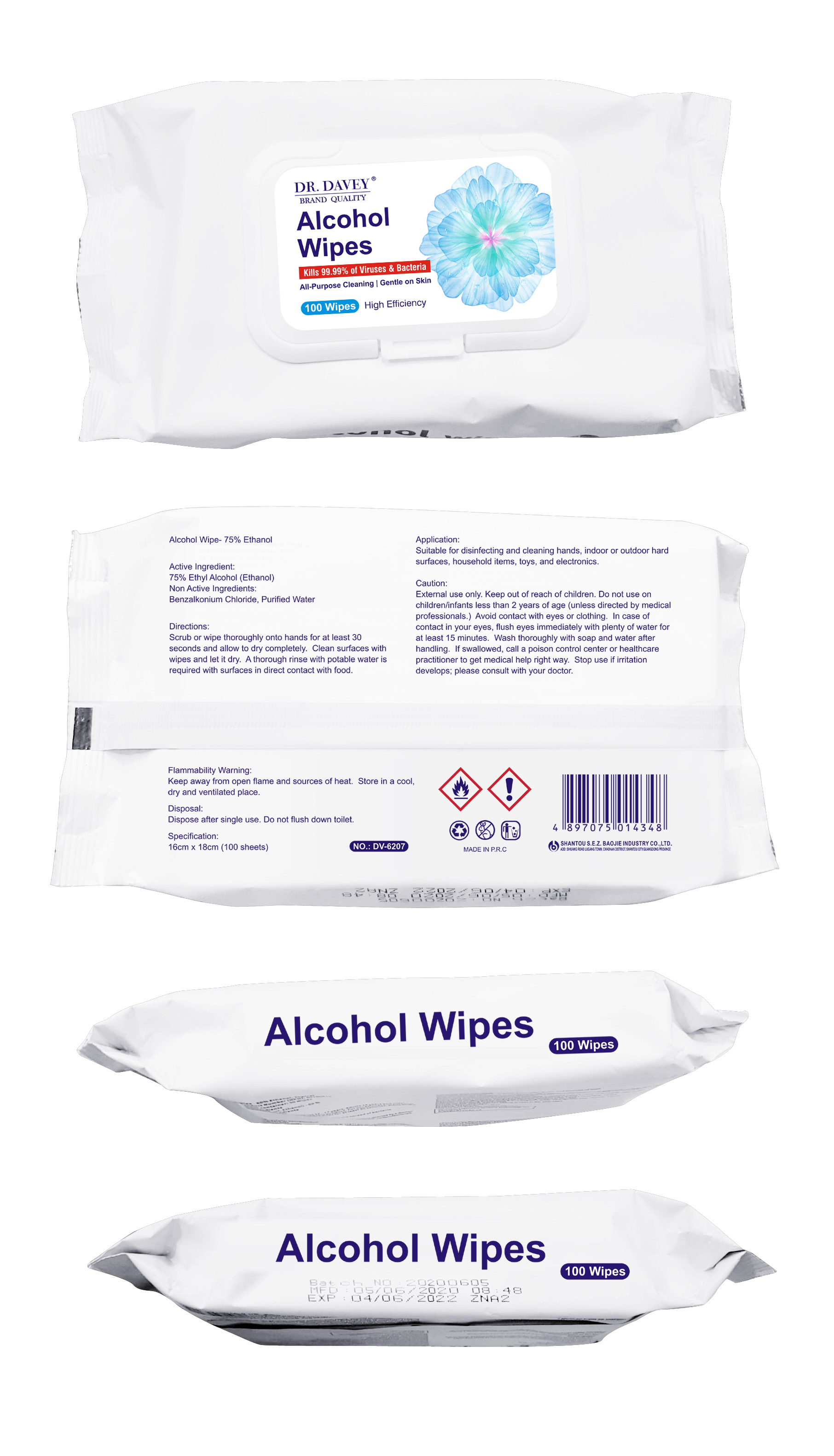 DRUG LABEL: Dr.Davey 75% alcohol wipes Step Solutions LLC Duns105607561
NDC: 74913-111 | Form: CLOTH
Manufacturer: SHANTOU S.E.Z BAOJIE INDUSTRY CO., LTD
Category: otc | Type: HUMAN OTC DRUG LABEL
Date: 20200620

ACTIVE INGREDIENTS: ALCOHOL 75 mL/100 U
INACTIVE INGREDIENTS: BENZALKONIUM CHLORIDE 0.03 mL/100 U; WATER 24.97 mL/100 U

Dr.Davey 75% ALCOHOL WIPES IMPORTER:CNEE Step Solutions LLC 13709 S WEST BAY SHORE DR.TRAVERSE CITY MI 49684,USA EIN/IRO#37-1863517 IMPORT#46-322643400